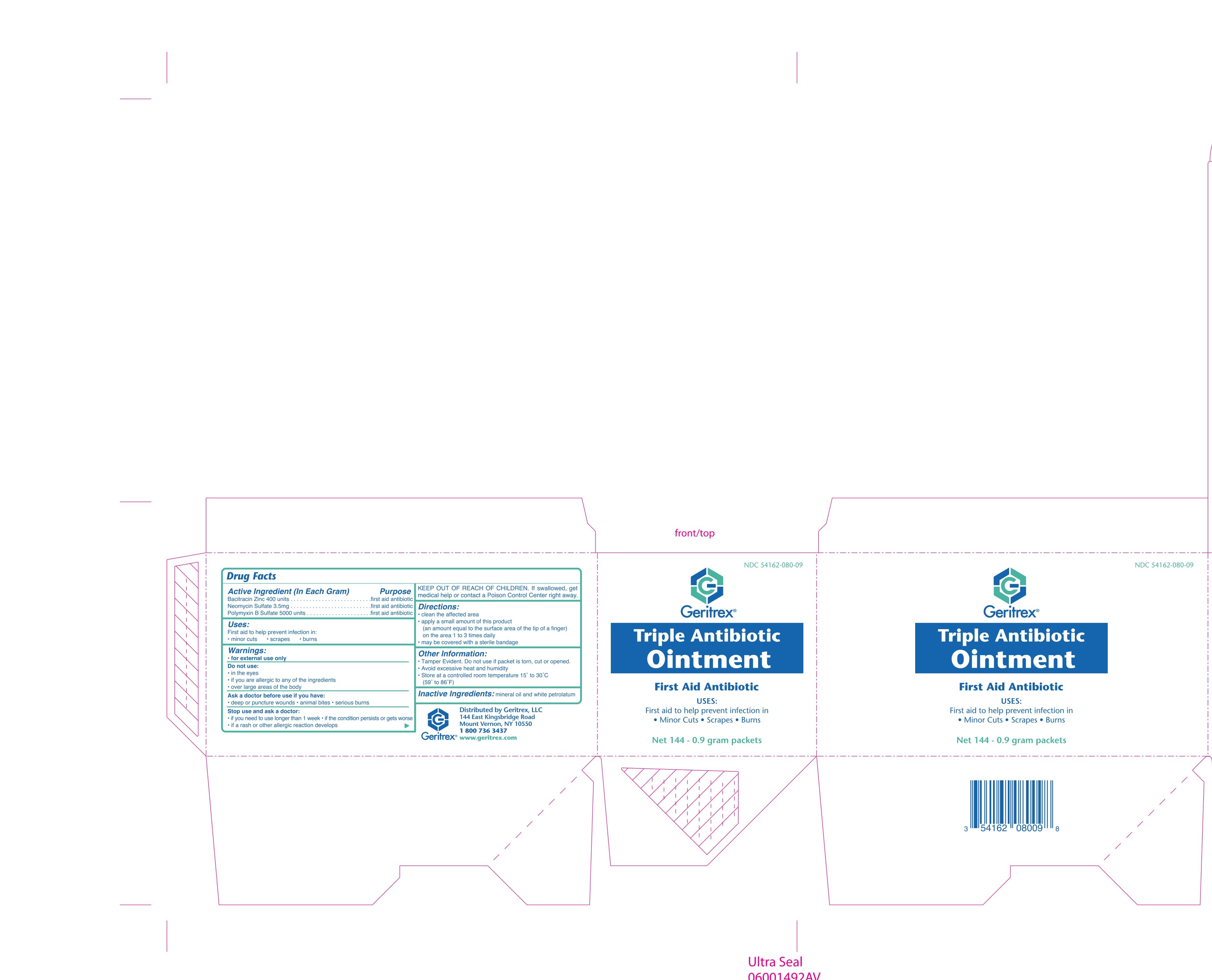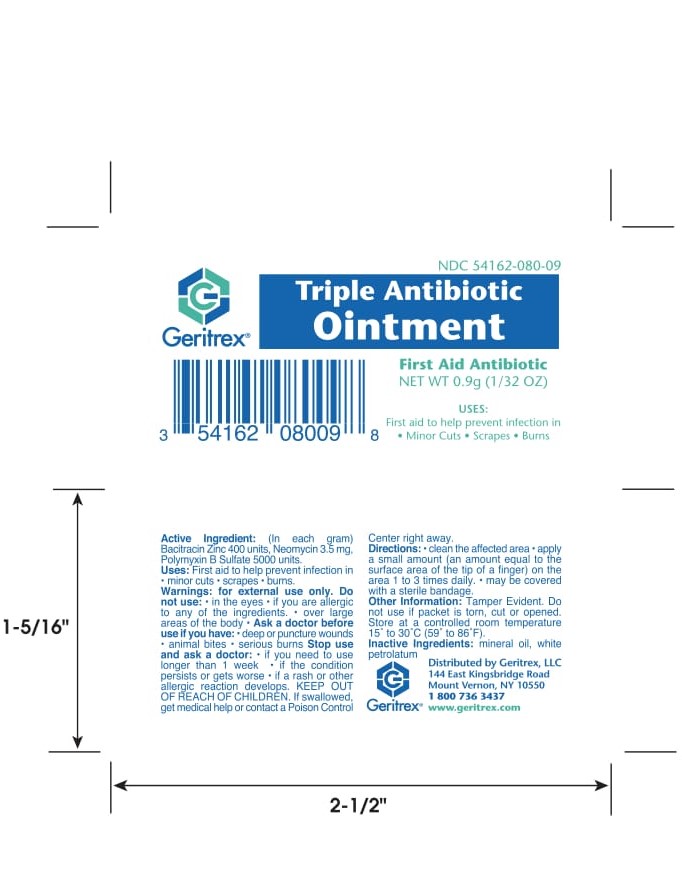 DRUG LABEL: Triple Antibiotic GRX
NDC: 54162-080 | Form: OINTMENT
Manufacturer: Geritrex LLC
Category: otc | Type: HUMAN OTC DRUG LABEL
Date: 20171201

ACTIVE INGREDIENTS: Bacitracin Zinc 400 [iU]/1 g; Neomycin Sulfate 3.5 mg/1 g; Polymyxin B Sulfate 5000 [iU]/1 g
INACTIVE INGREDIENTS: MINERAL OIL; Petrolatum

Triple Antibiotic GRX

Drug Facts

ACTIVE INGREDIENT

Active ingredients (in each gram) | Purpose
Bacitracin 400 units | First aid antibiotic
Neomycin 3.5 mg | First aid antibiotic
Polymyxin B 5,000 units | First aid antibiotic

Use

first aid to help prevent infection in minor:

- cuts
- scrapes
- burns

Warnings

For external use only.

Do not use

- if you are allergic to any of the ingredients
- in the eyes
- over large areas of the body

Ask a doctor before use if you have

- deep or puncture wounds
- animal bites
- serious burns

Stop use and ask a doctor if

- you need to use longer than 1 week
- condition persists or gets worse
- rash or other allergic reaction develops

Keep out of reach of children. If swallowed, get medical help or contact a Poison Control Center right away.

Directions

- clean the affected area
- apply a small amount of this product (an amount equal to the surface area of the tip of a finger) on the area 1 to 3 times daily
- may be covered with a sterile bandage

Other information

- store at 15° to 30°C (59° to 86° F)

Inactive ingredients

Mineral oil, petrolatum

Questions?

call 1-800-736-3437